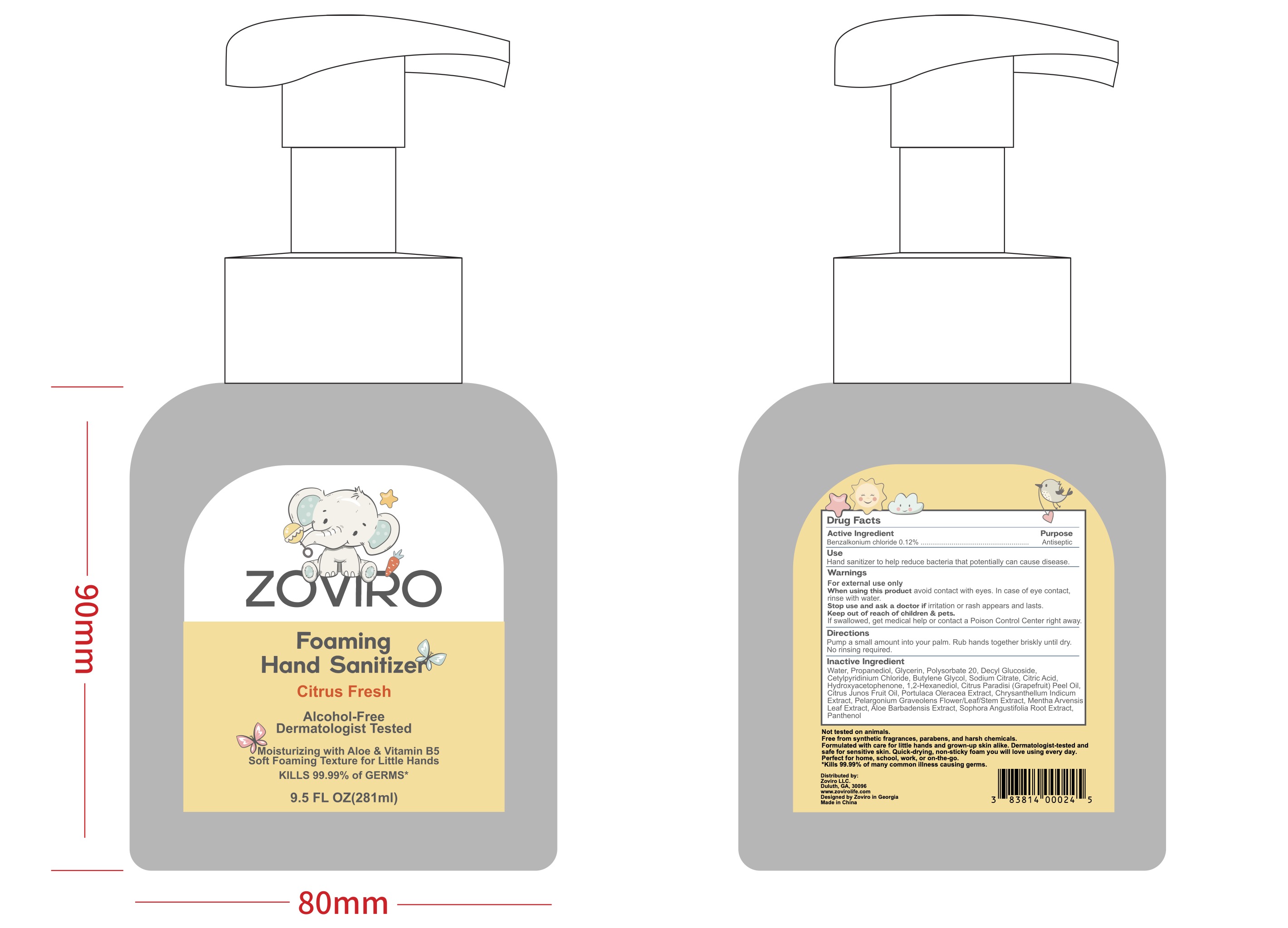 DRUG LABEL: Zoviro
NDC: 83814-006 | Form: LIQUID
Manufacturer: Zoviro, LLC
Category: otc | Type: HUMAN OTC DRUG LABEL
Date: 20251006

ACTIVE INGREDIENTS: BENZALKONIUM CHLORIDE 0.12 g/100 mL
INACTIVE INGREDIENTS: 1,2-HEXANEDIOL; PROPANEDIOL; HYDROXYACETOPHENONE; CETYLPYRIDINIUM CHLORIDE; SODIUM CITRATE; SOPHORA FLAVESCENS ROOT; CHRYSANTHELLUM INDICUM TOP; GLYCERIN; DECYL GLUCOSIDE; ALOE BARBADENSIS LEAF JUICE; MENTHA ARVENSIS LEAF; CITRUS PARADISI (GRAPEFRUIT) PEEL OIL; POLYSORBATE 20; PELARGONIUM GRAVEOLENS FLOWERING TOP; PURSLANE; CITRIC ACID; BUTYLENE GLYCOL; WATER; CITRUS JUNOS FRUIT OIL; PANTHENOL

Zoviro Foaming Hand Sanitizer, 9.5 oz Pump Bottle, Alcohol Free, Citrus Fresh Scent

Active Ingredient

Benzalkonium chloride 0.12%

Purpose

Antiseptic

Use

Hand sanitizer to help reduce bacteria that potentially can cause disease.

Warnings

For external use only

When using this product

avoid contact with eyes. In case of eye contact, rinse with water.

Keep out of reach of children & pets

If swallowed, get medical help or contact a Poison Control Center right away.

Directions

Pump a small amount into your palm. Rub hands together briskly until dry.

No rinsing required.

Inactive Ingredient

Water, Propanediol, Glycerin, Polysorbate 20, Decyl Glucoside, Cetylpyridinium Chloride, Butylene Glycol, Sodium Citrate, Citric Acid, Hydroxyacetophenone, 1,2-Hexanediol, Citrus Paradisi (Grapefruit) Peel Oil, Citrus Junos Fruit Oil, Portulaca Oleracea Extract, Chrysanthellum Indicum Extract, Pelargonium Graveolens Flower/Leaf/Stem Extract, Mentha Arvensis Leaf Extract, Aloe Barbadensis Extract, Sophora Angustifolia Root Extract, Panthenol